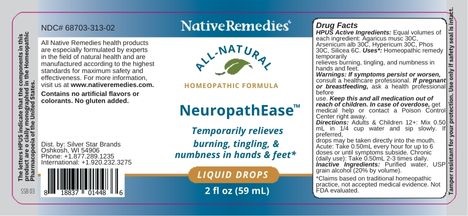 DRUG LABEL: NeuropathEase
NDC: 68703-313 | Form: LIQUID
Manufacturer: Silver Star Brands
Category: homeopathic | Type: HUMAN OTC DRUG LABEL
Date: 20250101

ACTIVE INGREDIENTS: AMANITA MUSCARIA FRUITING BODY 30 [hp_C]/59 mL; ARSENIC TRIOXIDE 30 [hp_C]/59 mL; HYPERICUM PERFORATUM 30 [hp_C]/59 mL; PHOSPHORUS 30 [hp_C]/59 mL; SILICON DIOXIDE 6 [hp_C]/59 mL
INACTIVE INGREDIENTS: ALCOHOL; WATER

NativeRemedies® NeuropathEase™

HPUS** Active Ingredients: Equal volumes of each ingredient: Agaricus musc 30C, Arsenicum alb 30C, Hypericum 30C, Phos 30C, Silicea 6C.

**"HPUS" indicates that the components in this product are official monographed in the Homeopathic Pharmacopoeia of the United States.

Uses*

Uses*: Homeopathic remedy temporarily relieves burning, tingling, and numbness in hands and feet.

*Claims based on traditional homeopathic practice, not accepted medical evidence. Not FDA evaluated.

Warnings

If symptoms persist or worsen, consult a healthcare professional. If pregnant or breastfeeding, ask a health professional before use. Keep this and all medication out of reach of children. In case of overdose, get medical help or contact a Poison Control Center right away.

Directions

Aduldts & Children 12+: Mix 0.50 mL in 1/4 cup water and sip slowly. If preferred, drops may be taken directly into the mouth. Acute: Take 0.50mL every hour for up to 6 doses or until symptoms subside. Chronic (daily use): Take 0.50mL 2-3 times daily.

OTHER SAFETY INFORMATION

All Native Remedies health products are especially formulated by experts in the field of natural health and are manufactured according to the highest pharmaceutical standards for maximum safety and effectiveness. For more information, visit us at www.nativeremedies.com.

Contains no artificial flavors or colorants. No gluten added.

Tamper resistant for your protection. Use only if safety seal is intact.

Inactive Ingredients

USP grain alcohol (20% by volume), purified water

KEEP OUT OF REACH OF CHILDREN

Keep this and all medication out of reach of children. In case of overdose, get medical help or contact a Poison Control Center right away.

PREGNANCY OR BREAST FEEDING

If pregnant or breastfeeding, ask a health professional before use.

PURPOSE

Temporarily relieves burning, tingling, & numbness in hands & feet.